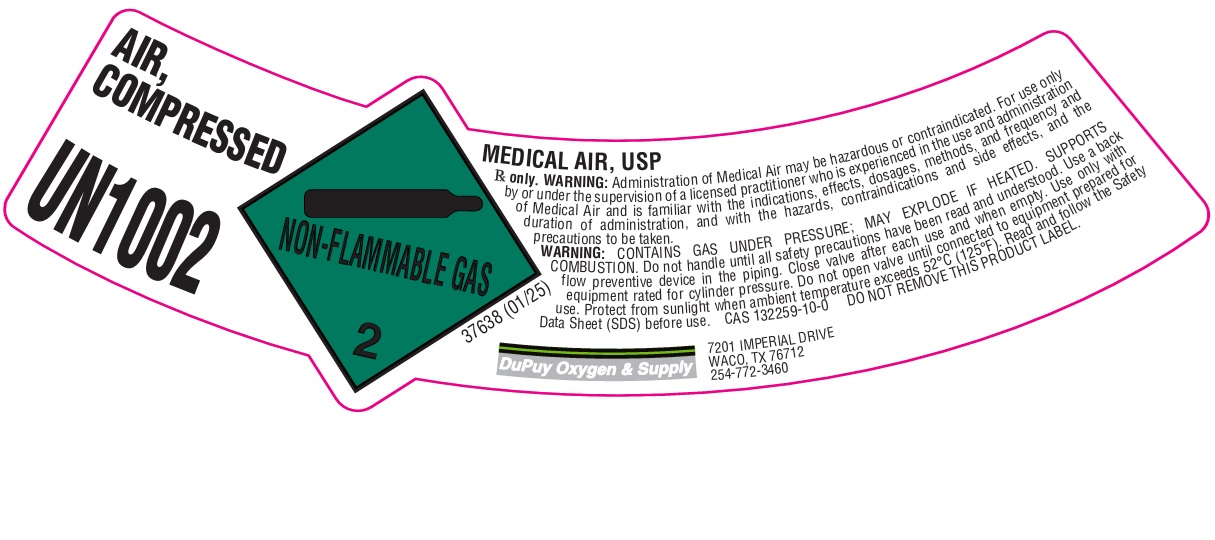 DRUG LABEL: Air
NDC: 50554-077 | Form: GAS
Manufacturer: DuPuy Oxygen & Supply Company, Inc.
Category: animal | Type: PRESCRIPTION ANIMAL DRUG LABEL
Date: 20251024

ACTIVE INGREDIENTS: AIR 1000 mL/1 L

Air

PACKAGE LABEL

AIR, COMPRESSED
UN1002
MEDICAL AIR, USP
Rx only. WARNING: Administration of Medical Air may be hazardous or contaminated. For use only by or under the supervision of a licensed practitioner who is experienced in the use and administration of Medical Air and is familiar with the indications, effects, dosages, methods, and frequency and duration of administration, and with the hazards, contraindications and side effects, and the precautions to be taken.
WARNING: CONTAINS GAS UNDER PRESSURE; MAY EXPLODE IF HEATED. SUPPORTS COMBUSTION. Do not handle until all safety precautions have been read and understood. Use a back flow preventive device in the piping. Close valve after each use and when empty. Use only with equipment rated for cylinder pressure. Do not open valve until connected to equipment prepared for use. Protect from sunlight when ambient temperature exceeds 52 C (125 F). Read and follow the Safety Data Sheet (SDS) before use. CAS 132259-10-0 DO NOT REMOVE THIS PRODUCT LABEL.
DuPuy Oxygen & Supply
7201 IMPERIAL DRIVE
WACO, TX 76712
254-772-3460